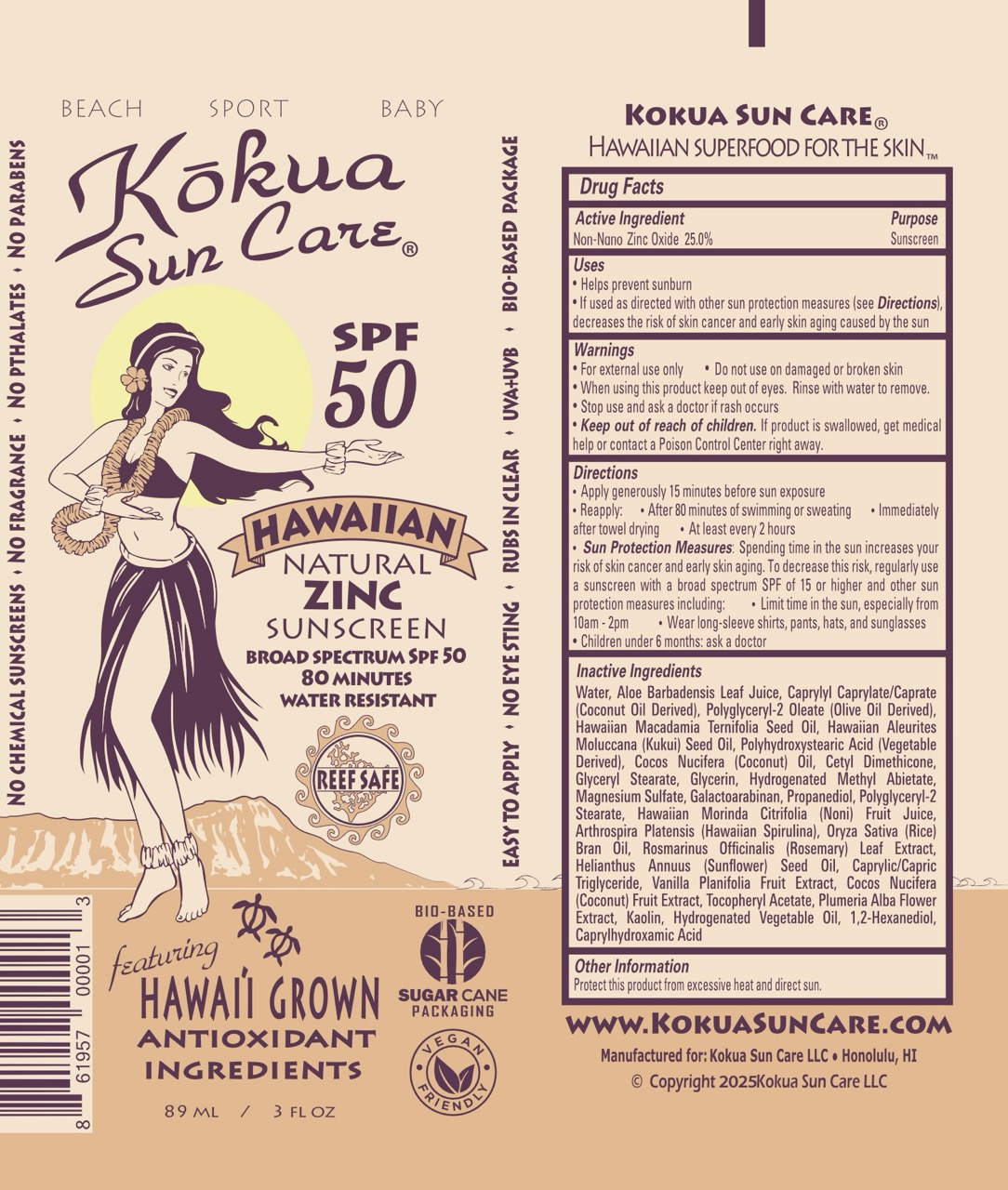 DRUG LABEL: Hawaiian Natural Zinc Sunscreen SPF 50
NDC: 72096-101 | Form: LOTION
Manufacturer: Kokua Sun Care
Category: otc | Type: HUMAN OTC DRUG LABEL
Date: 20251229

ACTIVE INGREDIENTS: ZINC OXIDE 25 g/100 g
INACTIVE INGREDIENTS: POLYGLYCERYL-2 OLEATE; GLYCERYL STEARATE; POLYGLYCERYL-2 STEARATE; NONI FRUIT JUICE; ARTHROSPIRA PLATENSIS; RICE BRAN; ROSEMARY; ALPHA-TOCOPHEROL ACETATE; CAPRYLHYDROXAMIC ACID; MEDIUM-CHAIN TRIGLYCERIDES; KAOLIN; 1,2-HEXANEDIOL; GALACTOARABINAN; MACADAMIA OIL; COCONUT OIL; GLYCERIN; WATER; ALOE VERA LEAF JUICE; KUKUI NUT OIL; PLUMERIA ALBA FLOWER; CETYL DIMETHICONE 25; MAGNESIUM SULFATE; COCONUT; SUNFLOWER OIL; VANILLA PLANIFOLIA FRUIT; CAPRYLYL CAPRYLATE/CAPRATE; POLYHYDROXYSTEARIC ACID (2300 MW); HYDROGENATED METHYL ABIETATE; PROPANEDIOL

Kokua Hawaiian Natural Zinc Sunscreen SPF 50 (89 ml / 3 fl oz) (30 ml / 1 fl oz)

Active Ingredient Purpose

Zinc Oxide 25% Sunscreen

Uses

- Helps prevent sunburn
- If used as directed with other sun protection measures (see Directions), Decreases the risk of skin cancer and early skin aging caused by the sun.

Keep out of reach of children.If product is swallowed, get medical help or contact a Poison Control Center right away.

Stop use and ask a doctor if rash occurs

Warnings:

- For external use only
- Do not use or broken skin
- When using this product keep out of eyes

Directions

- Apply generously 15 minutes before sun exposure
- Reapply:
- After 80 minutes if swimming or sweating
- Immediately after towel drying
- At least every 2 hours
- Sun Protection Measures: Spending time in the sun increases your risk of skin cancer and early skin aging. To decrease this risk, regularly use a sunscreen with a broad spectrum SPF of 15 or higher and other sun protection measures including:
- Limit time in the sun, especially from 10 am-2pm.
- Wear long-sleeve shirts, pants, hats, and sunglasses.
- Children under 6 months: ask a doctor.

Inactive Ingredients

Water (Aqua), Aloe Barbadensis Leaf Juice, Caprylyl Caprylate/Caprate, Polyglyceryl-2 Oleate, Macadamia Ternifolia Seed (Macadamia) Oil, Aleurites Moluccana Seed (Kukui) Oil, Polyhydroxystearic Acid, Cocos Nucifera (Coconut) Oil, Cetyl Dimethicone, Glyceryl Stearate, Glycerin, Hydrogenated Methyl Abietate, Magnesium Sulfate, Galactoarabinan, Propanediol, Polyglyceryl-2 Stearate, Morinda Citrifolia (Noni) Fruit Juice, Arthrospira Platensis (Hawaiian Spirulina), Oryza Sativa (Rice) Bran Extract, Rosmarinus Officinalis (Rosemary) Leaf Extract, Helianthus Annuus (Sunflower) Seed Extract, Caprylic/Capric Triglyceride, Vanilla Planifolia Fruit Extract, Cocos Nucifera (Coconut) Fruit Extract, Tocopheryl Acetate, Plumeria Alba Flower Extract, Kaolin, Hydrogenated Vegetable Oil, 1,2-Hexanediol, Caprylhydroxamic Acid.

Principal Display Panel

Hawaiian Natural Zinc Sunscreen

Broad Spectrum SPF 50

Water Resistant 80 minutes

89 mL / 3 FL OZ